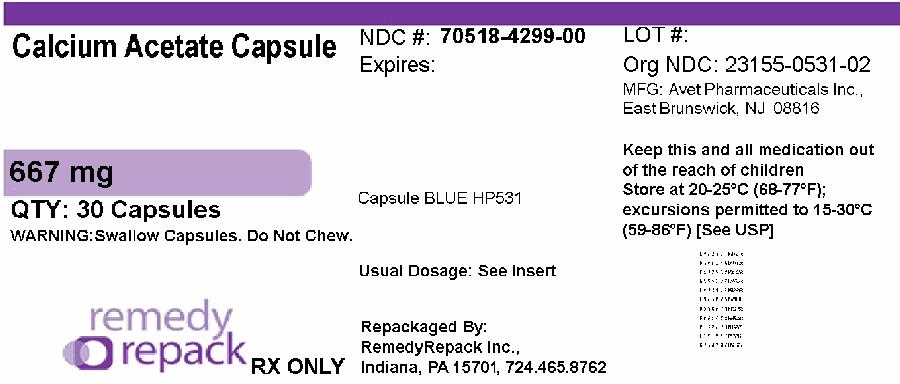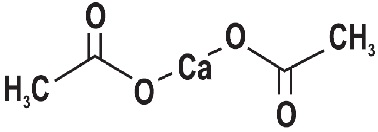 DRUG LABEL: calcium acetate
NDC: 70518-4299 | Form: CAPSULE
Manufacturer: REMEDYREPACK INC.
Category: prescription | Type: HUMAN PRESCRIPTION DRUG LABEL
Date: 20251002

ACTIVE INGREDIENTS: CALCIUM ACETATE 667 mg/1 1
INACTIVE INGREDIENTS: MAGNESIUM STEARATE; SODIUM LAURYL SULFATE; FD&C BLUE NO. 1; TITANIUM DIOXIDE; GELATIN; BUTYL ALCOHOL; PROPYLENE GLYCOL; SHELLAC; FERROSOFERRIC OXIDE; CROSPOVIDONE (120 .MU.M); FD&C RED NO. 3

HIGHLIGHTS OF PRESCRIBING INFORMATION

These highlights do not include all the information needed to use CALCIUM ACETATE Capsules safely and effectively. See full prescribing information for Calcium Acetate Capsules.
CALCIUM ACETATE capsules, 667 mg, for oral use.
Initial U.S. Approval: 1990

1 INDICATIONS AND USAGE

- Calcium acetate capsule is a phosphate binder indicated for the reduction of serum phosphorus in patients with end stage renal disease. (1)

2 DOSAGE AND ADMINISTRATION

- Starting dose is 2 capsules with each meal. (2)
- Titrate the dose every 2 to 3 weeks until acceptable serum phosphorus level is reached. Most patients require 3 to 4 capsules with each meal.(2)

3 DOSAGE FORMS AND STRENGTHS

- Capsule: 667 mg calcium acetate capsule.(3)

4 CONTRAINDICATIONS

- Hypercalcemia. (4)

5 WARNINGS AND PRECAUTIONS

- Treat mild hypercalcemia by reducing or interrupting calcium acetate and Vitamin D. Severe hypercalcemia may require hemodialysis and discontinuation of calcium acetate capsules. (5.1)
- Hypercalcemia may aggravate digitalis toxicity. (5.2)

6 ADVERSE REACTIONS

- The most common (>10%) adverse reactions are hypercalcemia, nausea, and vomiting. (6.1).
- In clinical studies, patients have occasionally experienced nausea during calcium acetate therapy. (6).

To report SUSPECTED ADVERSE REACTIONS, contact Avet Pharmaceuticals Inc. at 1-866-901-DRUG (3784) or FDA at 1-800-FDA-1088 or www.fda.gov/medwatch.

7 DRUG INTERACTIONS

- Calcium acetate capsule may decrease the bioavailability of tetracyclines or fluoroquinolones .(7)
- When clinically significant drug interactions are expected, administer the drug at least one hour before or at least three hours after calcium acetate capsule, or consider monitoring blood levels of the drug. (7)

FULL PRESCRIBING INFORMATION

1 INDICATIONS AND USAGE

Calcium acetate capsule is a phosphate binder indicated to reduce serum phosphorus in patients with end stage renal disease (ESRD).

2 DOSAGE AND ADMINISTRATION

The recommended initial dose of calcium acetate capsules for the adult dialysis patient is 2 capsules with each meal. Increase the dose gradually to lower serum phosphorus levels to the target range, as long as hypercalcemia does not develop. Most patients require 3-4 capsules with each meal.

3 DOSAGE FORMS AND STRENGTHS

Capsule: 667 mg calcium acetate per capsule.

4 CONTRAINDICATIONS

Patients with hypercalcemia.

5 WARNINGS AND PRECAUTIONS

5.1 Hypercalcemia

Patients with end stage renal disease may develop hypercalcemia when treated with calcium, including calcium acetate. Avoid the use of calcium supplements, including calcium-based nonprescription antacids, concurrently with calcium acetate.

An overdose of calcium acetate may lead to progressive hypercalcemia, which may require emergency measures. Therefore, early in the treatment phase during the dosage adjustment period, monitor serum calcium levels twice weekly. Should hypercalcemia develop, reduce the calcium acetate dosage or discontinue the treatment, depending on the severity of hypercalcemia.

More severe hypercalcemia (Ca>12 mg/dL) is associated with confusion, delirium, stupor and coma. Severe hypercalcemia can be treated by acute hemodialysis and discontinuing calcium acetate therapy.

Mild hypercalcemia (10.5 to 11.9 mg/dL) may be asymptomatic or manifest as constipation, anorexia, nausea, and vomiting. Mild hypercalcemia is usually controlled by reducing the calcium acetate dose or temporarily discontinuing therapy. Decreasing or discontinuing Vitamin D therapy is recommended as well.

Chronic hypercalcemia may lead to vascular calcification and other soft-tissue calcification. Radiographic evaluation of suspected anatomical regions may be helpful in early detection of soft tissue calcification. The long term effect of calcium acetate on the progression of vascular or soft tissue calcification has not been determined.

Hypercalcemia (>11 mg/dL) was reported in 16% of patients in a 3-month study of a solid dose formulation of calcium acetate; all cases resolved upon lowering the dose or discontinuing treatment.

Maintain the serum calcium-phosphorus (Ca x P) product below 55 mg^2/dL^2.

5.2 Concomitant Use with Medications

Hypercalcemia may aggravate digitalis toxicity.

6 ADVERSE REACTIONS

Hypercalcemia is discussed elsewhere [see Warnings and Precautions (5.1)].

6.1 Clinical Trial Experience

Because clinical trials are conducted under widely varying conditions, adverse reaction rates observed in the clinical trials of a drug cannot be directly compared to rates in the clinical trials of another drug and may not reflect the rates observed in practice.

In clinical studies, calcium acetate has been generally well tolerated.

Calcium acetate was studied in a 3-month, open-label, non-randomized study of 98 enrolled ESRD hemodialysis patients and in a two week double-blind, placebo-controlled, cross-over study with 69 enrolled ESRD hemodialysis patients. Adverse reactions (>2% on treatment) from these trials are presented in Table 1.

Table 1: Adverse Reactions in Patients with End-Stage Renal Disease Undergoing Hemodialysis
Preferred Term | Total adverse reactions reported for calcium acetate | 3 – mo, open-label study of calcium acetate n = 98 | Double-blind, placebo-controlled, cross over study of calcium acetate n = 69
 | n = 167 n (%) | n (%) | Calcium acetate n (%) | Placebo n (%)
Nausea | 6 (3.6) | 6 (6.1) | 0 (0.0) | 0 (0.0)
Vomiting | 4 (2.4) | 4 (4.1) | 0 (0.0) | 0 (0.0)
Hypercalcemia | 21 (12.6) | 16 (16.3) | 5 (7.2) | 0 (0.0)

Mild hypercalcemia may be asymptomatic or manifest itself as constipation, anorexia, nausea, and vomiting. More severe hypercalcemia is associated with confusion, delirium, stupor, and coma. Decreasing dialysate calcium concentration could reduce the incidence and severity of calcium acetate-induced hypercalcemia. Isolated cases of pruritus have been reported, which may represent allergic reactions.

6.2 Postmarketing Experience

Because these reactions are reported voluntarily from a population of uncertain size, it is not always possible to estimate their frequency or to establish a causal relationship to drug exposure.

The following additional adverse reactions have been identified during post-approval of calcium acetate: dizziness, edema, and weakness.

7 DRUG INTERACTIONS

The drug interaction of calcium acetate is characterized by the potential of calcium to bind to drugs with anionic functions (e.g., carboxyl and hydroxyl groups). Calcium acetate capsule may decrease the bioavailability of tetracyclines or fluoroquinolones via this mechanism.

There are no empirical data on avoiding drug interactions between calcium acetate and most concomitant drugs. When administering an oral medication with calcium acetate where a reduction in the bioavailability of that medication would have a clinically significant effect on its safety or efficacy, administer the drug one hour before or three hours after calcium acetate. Monitor blood levels of the concomitant drugs that have a narrow therapeutic range. Patients taking anti-arrhythmic medications for the control of arrhythmias and anti-seizure medications for the control of seizure disorders were excluded from the clinical trials with all forms of calcium acetate.

7.1 Ciprofloxacin

In a study of 15 healthy subjects, a co-administered single dose of 4 calcium acetate tablets approximately 2.7 g, decreased the bioavailability of ciprofloxacin by approximately 50%.

8 USE IN SPECIFIC POPULATIONS

8.1 PREGNANCY

Pregnancy Category C

Calcium acetate capsules contains calcium acetate. Animal reproduction studies have not been conducted with calcium acetate, and there are no adequate and well controlled studies of calcium acetate use in pregnant women. Patients with end stage renal disease may develop hypercalcemia with calcium acetate treatment [see Warnings and Precautions (5.1)] . Maintenance of normal serum calcium levels is important for maternal and fetal well being. Hypercalcemia during pregnancy may increase the risk for maternal and neonatal complications such as stillbirth, preterm delivery, and neonatal hypocalcemia and hypoparathyroidism. Calcium acetate treatment, as recommended, is not expected to harm a fetus if maternal calcium levels are properly monitored during and following treatment.

8.2 LABOR & DELIVERY

The effects of calcium acetate on labor and delivery are unknown.

8.3 NURSING MOTHERS

Calcium acetate capsule contains calcium acetate and is excreted in human milk. Human milk feeding by a mother receiving calcium acetate is not expected to harm an infant, provided maternal serum calcium levels are appropriately monitored.

8.4 PEDIATRIC USE

Safety and effectiveness in pediatric patients have not been established.

8.5 GERIATRIC USE

Clinical studies of calcium acetate did not include sufficient numbers of subjects aged 65 and over to determine whether they respond differently from younger subjects. Other clinical experience has not identified differences in responses between the elderly and younger patients. In general, dose selection for an elderly patient should be cautious, usually starting at the low end of the dosing range, reflecting the greater frequency of decreased hepatic, renal, or cardiac function, and of concomitant disease or other drug therapy.

10 OVERDOSAGE

Administration of calcium acetate capsule in excess of the appropriate daily dosage may result in hypercalcemia [see Warnings and Precautions (5.1)].

11 DESCRIPTION

Calcium acetate, USP acts as a phosphate binder. Its chemical name is calcium acetate. Its molecular formula is C4H6CaO4, and its molecular weight is 158.17. Its structural formula is:

Calcium acetate capsules, USP are hard gelatin capsules with blue opaque cap and body both imprinted "HP 531" in black ink. Each capsule contains 667 mg calcium acetate, USP (anhydrous; Ca(CH3COO)2; MW=158.17 grams) equal to 169 mg (8.45 mEq) calcium and following inactive ingredients crospovidone, FD&C Blue No. 1, FD&C Red No. 3, gelatin, magnesium stearate, sodium lauryl sulfate and titanium dioxide. In addition to the ingredients listed above, each capsule contains following inactive ingredients from imprinting ink: butyl alcohol, iron oxide black, propylene glycol and shellac.

FDA approved dissolution test specifications differ from USP.

12 CLINICAL PHARMACOLOGY

Patients with ESRD retain phosphorus and can develop hyperphosphatemia. High serum phosphorus can precipitate serum calcium resulting in ectopic calcification. Hyperphosphatemia also plays a role in the development of secondary hyperparathyroidism in patients with ESRD.

12.1 MECHANISM OF ACTION

Calcium acetate, when taken with meals, combines with dietary phosphate to form an insoluble calcium phosphate complex, which is excreted in the feces, resulting in decreased serum phosphorus concentration.

12.2 PHARMACODYNAMICS

Orally administered calcium acetate from pharmaceutical dosage forms is systemically absorbed up to approximately 40% under fasting conditions and up to approximately 30% under non-fasting conditions. This range represents data from both healthy subjects and renal dialysis patients under various conditions.

13 NONCLINICAL TOXICOLOGY

13.1 CARCINOGENESIS & MUTAGENESIS & IMPAIRMENT OF FERTILITY

No carcinogenicity, mutagenicity, or fertility studies have been conducted with calcium acetate.

14 CLINICAL STUDIES

Effectiveness of calcium acetate in decreasing serum phosphorus has been demonstrated in two studies of the calcium acetate solid dosage form.

Ninety-one patients with end-stage renal disease who were undergoing hemodialysis and were hyperphosphatemic (serum phosphorus >5.5 mg/dL) following a 1-week phosphate binder washout period contributed efficacy data to an open-label, non-randomized study.

The patients received calcium acetate 667 mg tablets at each meal for a period of 12 weeks. The initial starting dose was 2 tablets per meal for 3 meals a day, and the dose was adjusted as necessary to control serum phosphorus levels. The average final dose after 12 weeks of treatment was 3.4 tablets per meal. Although there was a decrease in serum phosphorus, in the absence of a control group the true magnitude of effect is uncertain.

The data presented in Table 2 demonstrate the efficacy of calcium acetate in the treatment of hyperphosphatemia in end-stage renal disease patients. The effects on serum calcium levels are also presented.

Table 2: Average Serum Phosphorous and Calcium Levels at Pre-Study, Interim and Study Completion Time points
Parameter | Pre-Study | Week 4b | Week 8 | Week 12 | p-valuec
Phosphorus (mg/dL) a | 7.4 ± 0.17 | 5.9 ± 0.16 | 5.6 ± 0.17 | 5.2 ± 0.17 | ≤0.01
Calcium (mg/dL) a | 8.9 ± 0.09 | 9.5 ± 0.10 | 9.7 ± 0.10 | 9.7 ± 0.10 | ≤0.01
aValues expressed as mean ± SE.
bNinety-one patients completed at least 6 weeks of the study.
cANOVA of difference in values at pre-study and study completion

There was a 30% decrease in serum phosphorus levels during the 12 week study period (p<0.01). Two-thirds of the decline occurred in the first month of the study. Serum calcium increased 9% during the study mostly in the first month of the study.

Treatment with the phosphate binder was discontinued for patients from the open-label study, and those patients whose serum phosphorus exceeded 5.5 mg/dL were eligible for entry into a double-blind, placebo-controlled, cross-over study. Patients were randomized to receive calcium acetate or placebo, and each continued to receive the same number of tablets as had been individually established during the previous study. Following 2 weeks of treatment, patients switched to the alternative therapy for an additional 2 weeks.

The phosphate binding effect of calcium acetate is shown in the Table 3.

16 HOW SUPPLIED/STORAGE AND HANDLING

Calcium Acetate Capsules, USP are blue opaque capsules imprinted with "HP 531" for oral administration containing 667 mg calcium acetate (anhydrous Ca(CH3COO)2; MW=158.17 grams) equal to 169 mg (8.45 mEq) calcium.

NDC: 70518-4299-00

PACKAGING: 30 in 1 BLISTER PACK

STORAGE: Store at 25°C (77°F); excursions permitted to 15 to 30°C (59 to 86°F) [See USP Controlled Room Temperature].

Repackaged and Distributed By:

Remedy Repack, Inc.

625 Kolter Dr. Suite #4 Indiana, PA 1-724-465-8762

17 PATIENT COUNSELING INFORMATION

Inform patients to take calcium acetate capsules with meals, adhere to their prescribed diets, and avoid the use of calcium supplements including nonprescription antacids. Inform the patients about the symptoms of hypercalcemia [see Warnings and Precautions (5.1)and Adverse Reactions (6.1)].

Advise patients who are taking an oral medication where reduction in the bioavailability of that medication would have clinically significant effect on its safety and efficacy to take the drug one hour before or three hours after calcium acetate capsules.

Repackaged By / Distributed By: RemedyRepack Inc.

625 Kolter Drive, Indiana, PA 15701

(724) 465-8762

PACKAGE LABEL

DRUG: calcium acetate

GENERIC: calcium acetate

DOSAGE: CAPSULE

ADMINSTRATION: ORAL

NDC: 70518-4299-0

COLOR: blue

SHAPE: CAPSULE

SCORE: No score

SIZE: 23 mm

IMPRINT: HP531

PACKAGING: 30 in 1 BLISTER PACK

ACTIVE INGREDIENT(S):

- CALCIUM ACETATE 667mg in 1

INACTIVE INGREDIENT(S):

- MAGNESIUM STEARATE
- SODIUM LAURYL SULFATE
- FD&C BLUE NO. 1
- TITANIUM DIOXIDE
- GELATIN
- BUTYL ALCOHOL
- PROPYLENE GLYCOL
- SHELLAC
- FERROSOFERRIC OXIDE
- CROSPOVIDONE (120 .MU.M)
- FD&C RED NO. 3